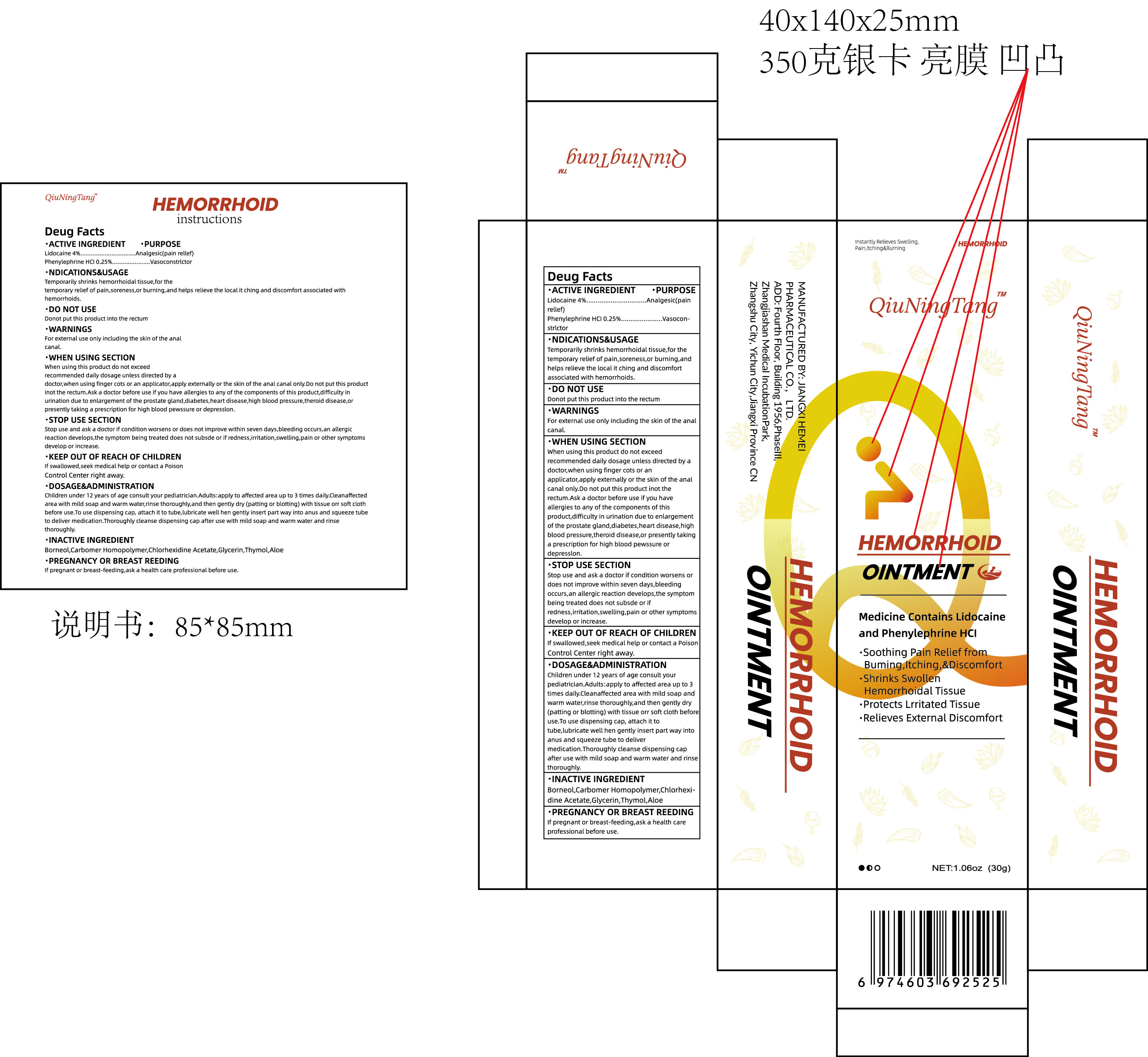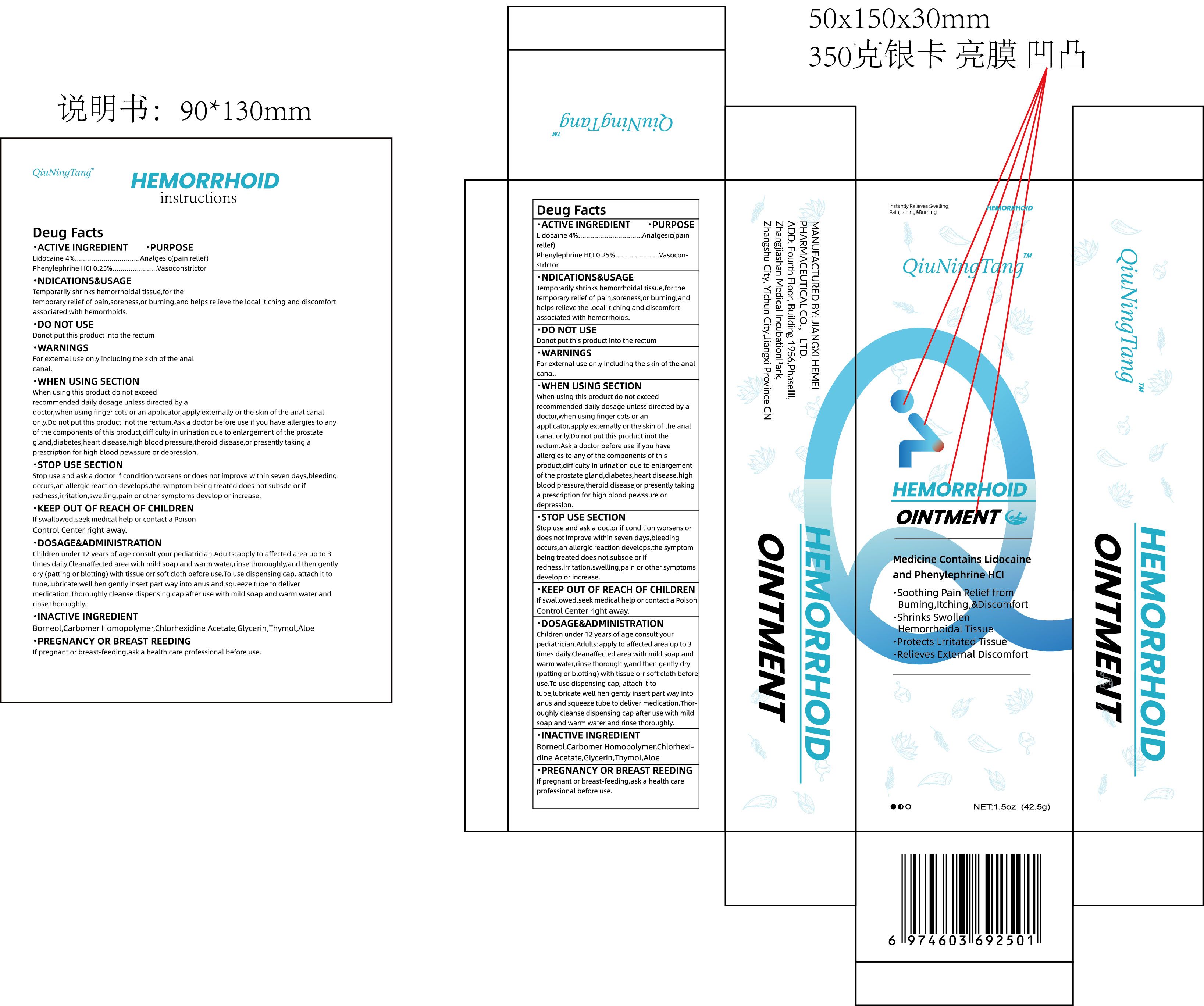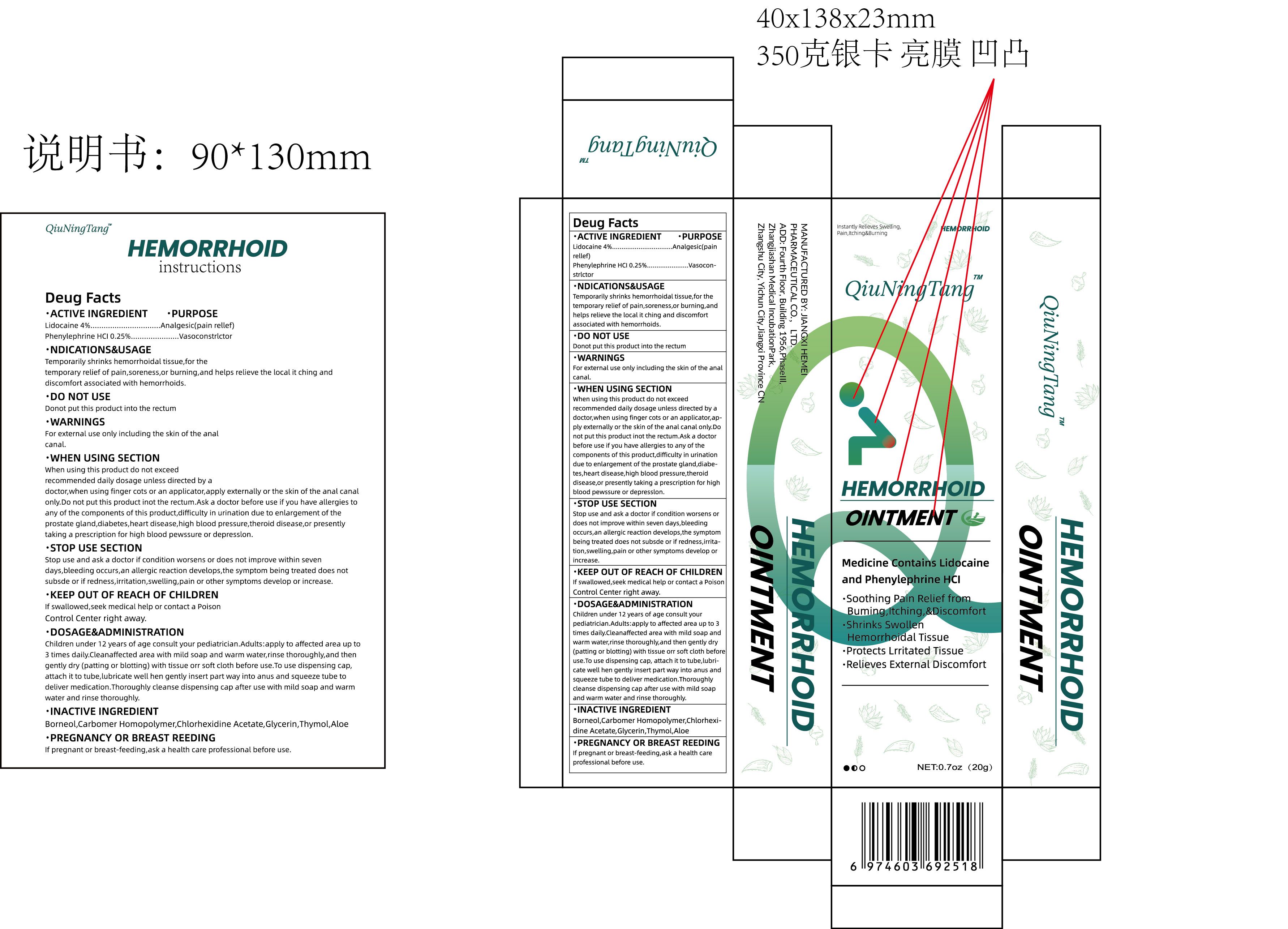 DRUG LABEL: QiuNingTang HEMORRHOID
NDC: 84010-037 | Form: OINTMENT
Manufacturer: Jiangxi Hemei Pharmaceutical Co., Ltd
Category: otc | Type: HUMAN OTC DRUG LABEL
Date: 20241016

ACTIVE INGREDIENTS: LIDOCAINE 4 g/100 g; PHENYLEPHRINE HYDROCHLORIDE 0.25 g/100 g
INACTIVE INGREDIENTS: CARBOMER HOMOPOLYMER, UNSPECIFIED TYPE; GLYCERIN; BORNEOL; THYMOL; ALOE; CHLORHEXIDINE ACETATE

84010-037

Active Ingredient

Lidocaine 4%

Phenylephrine HCI 0.25%

Purpose

Analgesic (pain relief) Vasoconstrictor

Use

Temporarily shrinks hemorrhoidal tissue,for the temporary relief of pain,soreness,or burning,and helps relieve the local it ching and discomfort associated with hemorrhoids.

Warnings

For external use only including the skin of the analcanal.

Do not use

Do not put this product into the rectum

When Using

When using this product do not exceed
recommended daily dosage unless directed by a doctor,when using finger cots or an applicator,apply externally or the skin of the anal canal only.Do not put this product inot the rectum.Ask a doctor before use if you have allergies to any of the components of this product,difficulty in urination due to enlargement of the prostate gland,diabetes,heart disease,high blood pressure,theroid disease,or presently taking a prescription for high blood pewssure or depresslon.

Stop Use

Stop use and ask a doctor if condition worsens or does not improve within seven days,bleeding occurs,an allergic reaction develops,the symptom being treated does not subsde or if redness,irritation,swelling,pain or other symptoms develop or increase.

Ask Doctor

Stop use and ask a doctor if condition worsens or does not improve within seven days, bleeding occurs, an allergic reaction develops, the symptom being treated does not subside or if redness, irritation, swelling, pain or other symptoms develop or increase.

Keep Oot Of Reach Of Children

If swallowed, seek medical help or contact a Poison Control Center right away.

Directions

Children under 12 years of age consult your pediatrician.Adults:apply to affected area up to 3times daily.Cleanaffected area with mild soap and warm water,rinse thoroughly, and then gentlydry (patting or blotting) with tissue orr soft cloth before use.To use dispensing cap, attach it totube,lubricate well hen gently insert part way into anus and squeeze tube to delivermedication.Thoroughly cleanse dispensing cap after use with mild soap and warm water andrinse thoroughly

Other information

If pregnant or breast-feeding, ask a health care professional before use.

Inactive ingredients

Borneol,Carbomer Homopolymer,Chlorhexidine Acetate,Glycerin, Thymol, Aloe